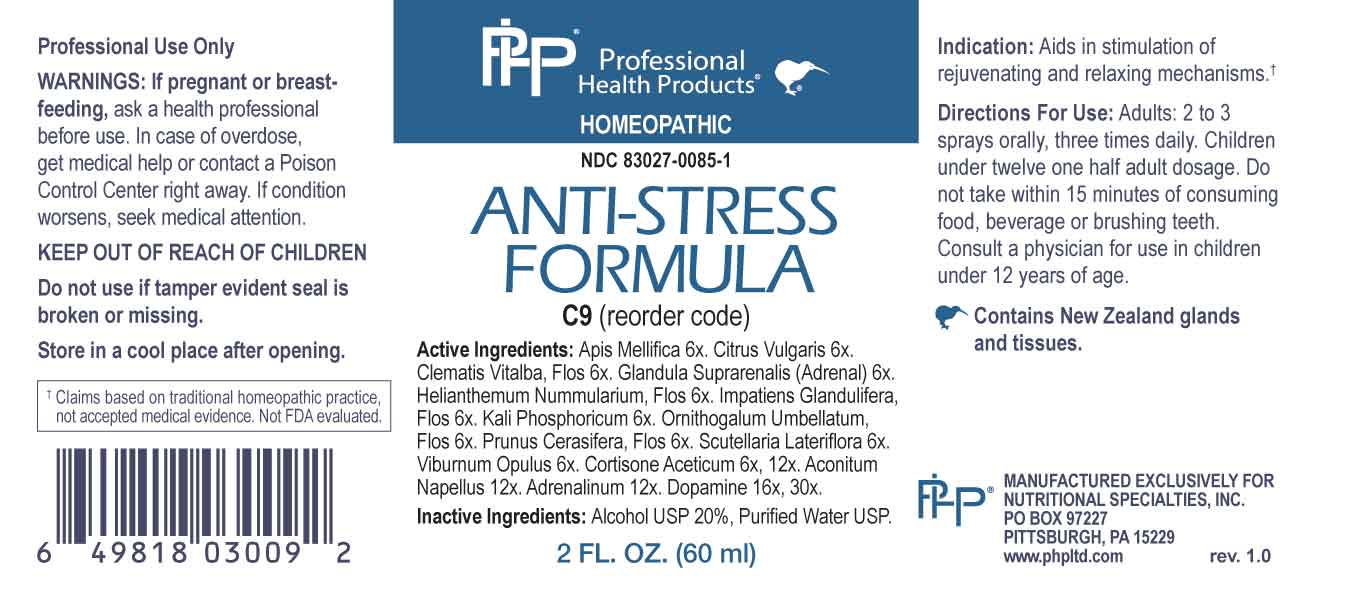 DRUG LABEL: Anti Stress Formula
NDC: 83027-0085 | Form: SPRAY
Manufacturer: Nutritional Specialties, Inc.
Category: homeopathic | Type: HUMAN OTC DRUG LABEL
Date: 20230725

ACTIVE INGREDIENTS: APIS MELLIFERA 6 [hp_X]/1 mL; CITRUS AURANTIUM FRUIT RIND 6 [hp_X]/1 mL; CLEMATIS VITALBA FLOWER 6 [hp_X]/1 mL; BOS TAURUS ADRENAL GLAND 6 [hp_X]/1 mL; HELIANTHEMUM NUMMULARIUM FLOWER 6 [hp_X]/1 mL; IMPATIENS GLANDULIFERA FLOWER 6 [hp_X]/1 mL; DIBASIC POTASSIUM PHOSPHATE 6 [hp_X]/1 mL; ORNITHOGALUM UMBELLATUM FLOWERING TOP 6 [hp_X]/1 mL; PRUNUS CERASIFERA FLOWER 6 [hp_X]/1 mL; SCUTELLARIA LATERIFLORA WHOLE 6 [hp_X]/1 mL; VIBURNUM OPULUS BARK 6 [hp_X]/1 mL; CORTISONE ACETATE 6 [hp_X]/1 mL; ACONITUM NAPELLUS WHOLE 12 [hp_X]/1 mL; EPINEPHRINE 12 [hp_X]/1 mL; DOPAMINE HYDROCHLORIDE 16 [hp_X]/1 mL
INACTIVE INGREDIENTS: WATER; ALCOHOL

DRUG FACTS:

ACTIVE INGREDIENTS:

Apis Mellifica 6X, Citrus Vulgaris 6X, Clematis Vitalba, Flos 6X, Glandula Suprarenalis (Adrenal) 6X, Helianthemum Nummularium, Flos 6X, Impatiens Glandulifera, Flos 6X, Kali Phosphoricum 6X, Ornithogalum Umbellatum, Flos 6X, Prunus Cerasifera, Flos 6X, Scutellaria Lateriflora 6X, Viburnum Opulus 6X, Cortisone Aceticum 6X, 12X, Aconitum Napellus 12X, Adrenalinum 12X, Dopamine 16X, 30X.

PURPOSE:

Aids in stimulation of rejuvenating and relaxing mechanisms.†

†Claims based on traditional homeopathic practice, not accepted medical evidence. Not FDA evaluated.

WARNINGS:

Professional Use Only

If pregnant or breast-feeding, ask a health professional before use.

In case of overdose, get medical help or contact a Poison Control Center right away.

If condition worsens, seek medical attention.

KEEP OUT OF REACH OF CHILDREN

Do not use if tamper evident seal is broken or missing.

Store in a cool place after opening

KEEP OUT OF REACH OF CHILDREN:

In case of overdose, get medical help or contact a Poison Control Center right away.

DIRECTIONS:

Adults: 2 to 3 sprays orally, three times daily. Children under twelve one half adult dosage. Do not take within 15 minutes of consuming food, beverage or brushing teeth. Consult a physician for use in children under 12 years of age.

INDICATIONS:

Aids in stimulation of rejuvenating and relaxing mechanisms.†

†Claims based on traditional homeopathic practice, not accepted medical evidence. Not FDA evaluated.

INACTIVE INGREDIENTS:

Alcohol USP 20%, Purified Water USP.

QUESTIONS:

MANUFACTURED EXCLUSIVELY FOR

NUTRITIONAL SPECIALTIES, INC.

PO BOX 97227

PITTSBURG, PA 15229

www.phpltd.com

PACKAGE LABEL DISPLAY:

Professional

Health Products

HOMEOPATHIC

NDC 83027-0085-1

ANTI-STRESS

FORMULA

2 FL. OZ (60 ml)